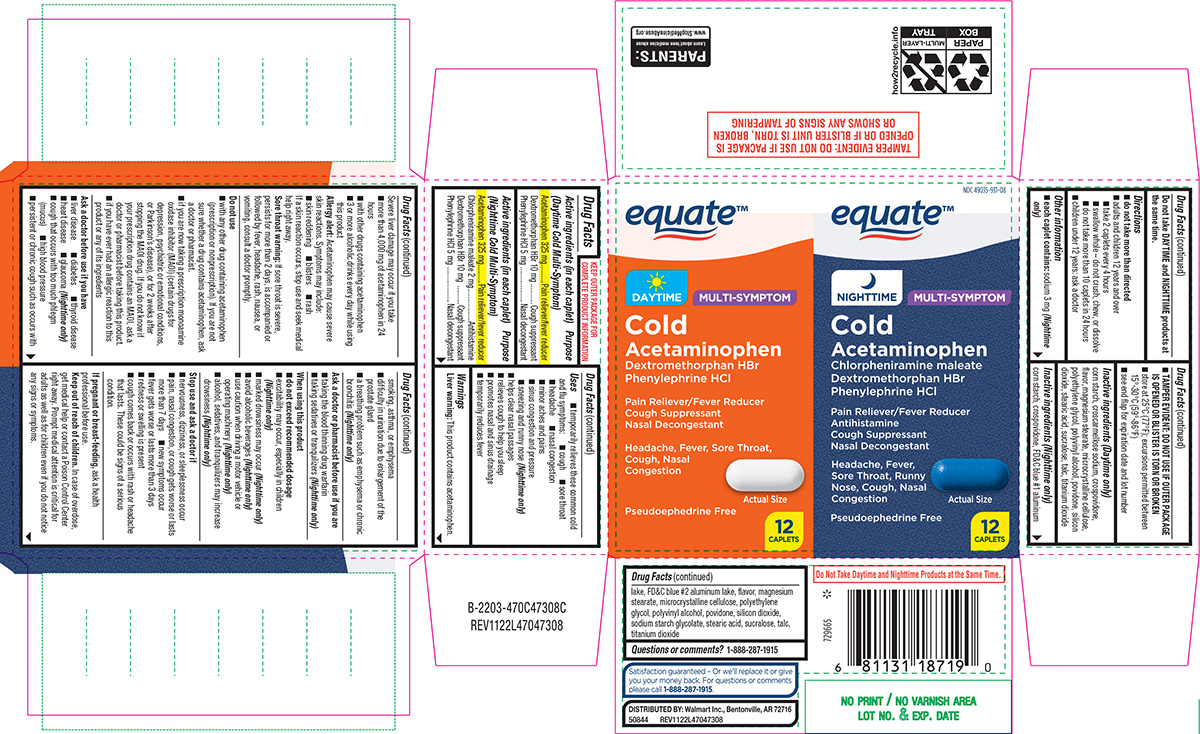 DRUG LABEL: Cold Multi-Symptom
NDC: 49035-931 | Form: KIT | Route: ORAL
Manufacturer: Wal-Mart Stores Inc
Category: otc | Type: HUMAN OTC DRUG LABEL
Date: 20260202

ACTIVE INGREDIENTS: ACETAMINOPHEN 325 mg/1 1; CHLORPHENIRAMINE MALEATE 2 mg/1 1; DEXTROMETHORPHAN HYDROBROMIDE 10 mg/1 1; PHENYLEPHRINE HYDROCHLORIDE 5 mg/1 1; ACETAMINOPHEN 325 mg/1 1; DEXTROMETHORPHAN HYDROBROMIDE 10 mg/1 1; PHENYLEPHRINE HYDROCHLORIDE 5 mg/1 1
INACTIVE INGREDIENTS: STARCH, CORN; CROSPOVIDONE, UNSPECIFIED; FD&C BLUE NO. 1 ALUMINUM LAKE; FD&C BLUE NO. 2 ALUMINUM LAKE; MAGNESIUM STEARATE; MICROCRYSTALLINE CELLULOSE; POLYETHYLENE GLYCOL, UNSPECIFIED; POLYVINYL ALCOHOL, UNSPECIFIED; POVIDONE, UNSPECIFIED; SILICON DIOXIDE; SODIUM STARCH GLYCOLATE TYPE A POTATO; STEARIC ACID; SUCRALOSE; TALC; TITANIUM DIOXIDE; STARCH, CORN; CROSCARMELLOSE SODIUM; CROSPOVIDONE, UNSPECIFIED; MAGNESIUM STEARATE; MICROCRYSTALLINE CELLULOSE; POLYETHYLENE GLYCOL, UNSPECIFIED; POLYVINYL ALCOHOL, UNSPECIFIED; POVIDONE, UNSPECIFIED; SILICON DIOXIDE; STEARIC ACID; SUCRALOSE; TALC; TITANIUM DIOXIDE

Equate 44-470C473-08

Active ingredients (in each caplet) (Daytime Cold Multi-Symptom)

Acetaminophen 325 mg
Dextromethorphan HBr 10 mg
Phenylephrine HCl 5 mg

Purpose

Pain reliever/fever reducer
Cough suppressant
Nasal decongestant

Active ingredients (in each caplet) (Nighttime Cold Multi-Symptom)

Acetaminophen 325 mg
Chlorpheniramine maleate 2 mg
Dextromethorphan HBr 10 mg
Phenylephrine HCl 5 mg

Purpose

Pain reliever/fever reducer
Antihistamine
Cough suppressant
Nasal decongestant

Uses

- temporarily relieves these common cold and flu symptoms:
  - cough
  - sore throat
  - headache
  - nasal congestion
  - minor aches and pains
  - sinus congestion and pressure
  - sneezing and runny nose (Nighttime only)
- helps clear nasal passages
- relieves cough to help you sleep
- promotes nasal and sinus drainage
- temporarily reduces fever

Warnings

Liver warning: This product contains acetaminophen. Severe liver damage may occur if you take

- more than 4,000 mg of acetaminophen in 24 hours
- with other drugs containing acetaminophen
- 3 or more alcoholic drinks every day while using this product

Allergy alert: Acetaminophen may cause severe skin reactions. Symptoms may include:

- skin reddening
- blisters
- rash

If a skin reaction occurs, stop use and seek medical help right away.

Sore throat warning: If sore throat is severe, persists for more than 2 days, is accompanied or followed by fever, headache, rash, nausea, or vomiting, consult a doctor promptly.

Do not use

- with any other drug containing acetaminophen (prescription or nonprescription). If you are not sure whether a drug contains acetaminophen, ask a doctor or pharmacist.
- if you are now taking a prescription monoamine oxidase inhibitor (MAOI) (certain drugs for depression, psychiatric or emotional conditions, or Parkinson’s disease), or for 2 weeks after stopping the MAOI drug. If you do not know if your prescription drug contains an MAOI, ask a doctor or pharmacist before taking this product.
- if you have ever had an allergic reaction to this product or any of its ingredients

Ask a doctor before use if you have

- liver disease
- diabetes
- thyroid disease
- heart disease
- glaucoma (Nighttime only)
- cough that occurs with too much phlegm (mucus)
- high blood pressure
- persistent or chronic cough such as occurs with smoking, asthma, or emphysema
- difficulty in urination due to enlargement of the prostate gland
- a breathing problem such as emphysema or chronic bronchitis (Nighttime only)

Ask a doctor or pharmacist before use if you are

- taking the blood thinning drug warfarin
- taking sedatives or tranquilizers (Nighttime only)

When using this product

- do not exceed recommended dosage
- excitability may occur, especially in children (Nighttime only)
- marked drowsiness may occur (Nighttime only)
- avoid alcoholic beverages (Nighttime only)
- use caution when driving a motor vehicle or operating machinery (Nighttime only)
- alcohol, sedatives, and tranquilizers may increase drowsiness (Nighttime only)

Stop use and ask a doctor if

- nervousness, dizziness, or sleeplessness occur
- pain, nasal congestion, or cough gets worse or lasts more than 7 days
- new symptoms occur
- fever gets worse or lasts more than 3 days
- redness or swelling is present
- cough comes back or occurs with rash or headache that lasts. These could be signs of a serious condition.

If pregnant or breast-feeding,

ask a health professional before use.

Keep out of reach of children.

In case of overdose, get medical help or contact a Poison Control Center right away. Prompt medical attention is critical for adults as well as for children even if you do not notice any signs or symptoms.

Do not take DAYTIME and NIGHTTIME products at the same time.

Directions

- do not take more than directed
- adults and children 12 years and over
  - take 2 caplets every 4 hours
  - swallow whole – do not crush, chew, or dissolve
  - do not take more than 10 caplets in 24 hours
- children under 12 years: ask a doctor

Other information

- each caplet contains: sodium 3 mg (Nighttime only)
- TAMPER EVIDENT: DO NOT USE IF OUTER PACKAGE IS OPENED OR BLISTER IS TORN OR BROKEN
- store at 25°C (77°F); excursions permitted between 15°-30°C (59°-86°F)
- see end flap for expiration date and lot number

Inactive ingredients (Daytime only)

corn starch, croscarmellose sodium, crospovidone, flavor, magnesium stearate, microcrystalline cellulose, polyethylene glycol, polyvinyl alcohol, povidone, silicon dioxide, stearic acid, sucralose, talc, titanium dioxide

Inactive ingredients (Nighttime only)

corn starch, crospovidone, FD&C blue #1 aluminum lake, FD&C blue #2 aluminum lake, flavor, magnesium stearate, microcrystalline cellulose, polyethylene glycol, polyvinyl alcohol, povidone, silicon dioxide, sodium starch glycolate, stearic acid, sucralose, talc, titanium dioxide

Questions or comments?

1-888-287-1915

Principal Display Panel

NDC 49035-931-08

equate™

DAYTIME

Multi-Symptom

Cold

Acetaminophen,
Dextromethorphan HBr,
Phenylephrine HCl

Pain Reliever/Fever reducer
Cough Suppressant
Nasal Decongestant

Headache, Fever, Sore Throat,
Cough, Nasal
Congestion

Actual Size

Pseudoephedrine Free

12
CAPLETS

NIGHTTIME

Multi-Symptom

Cold

Acetaminophen,
Chlorpheniramine maleate
Dextromethorphan HBr
Phenylephrine HCl

Pain Reliever/Fever Reducer
Antihistamine
Cough Suppressant
Nasal Decongestant

Headache, Fever,
Sore Throat, Runny
Nose, Cough, Nasal
Congestion

Actual Size

Pseudoephedrine Free

12
CAPLETS

TAMPER EVIDENT: DO NOT USE IF PACKAGE IS
OPENED OR IF BLISTER UNIT IS TORN, BROKEN
OR SHOWS ANY SIGNS OF TAMPERING

Do Not Take The Daytime and Nighttime Products at the Same Time.

Satisfaction guaranteed - Or we'll replace it or give
you your money back. For questions or comments
please call 1-888-287-1915.

DISTRIBUTED BY: Walmart Inc., Bentonville, AR 72716

50844 REV1122L47047308

PARENTS:
Learn about teen medicine abuse
www.StopMedicineAbuse.org

Equate 44-470C47308C